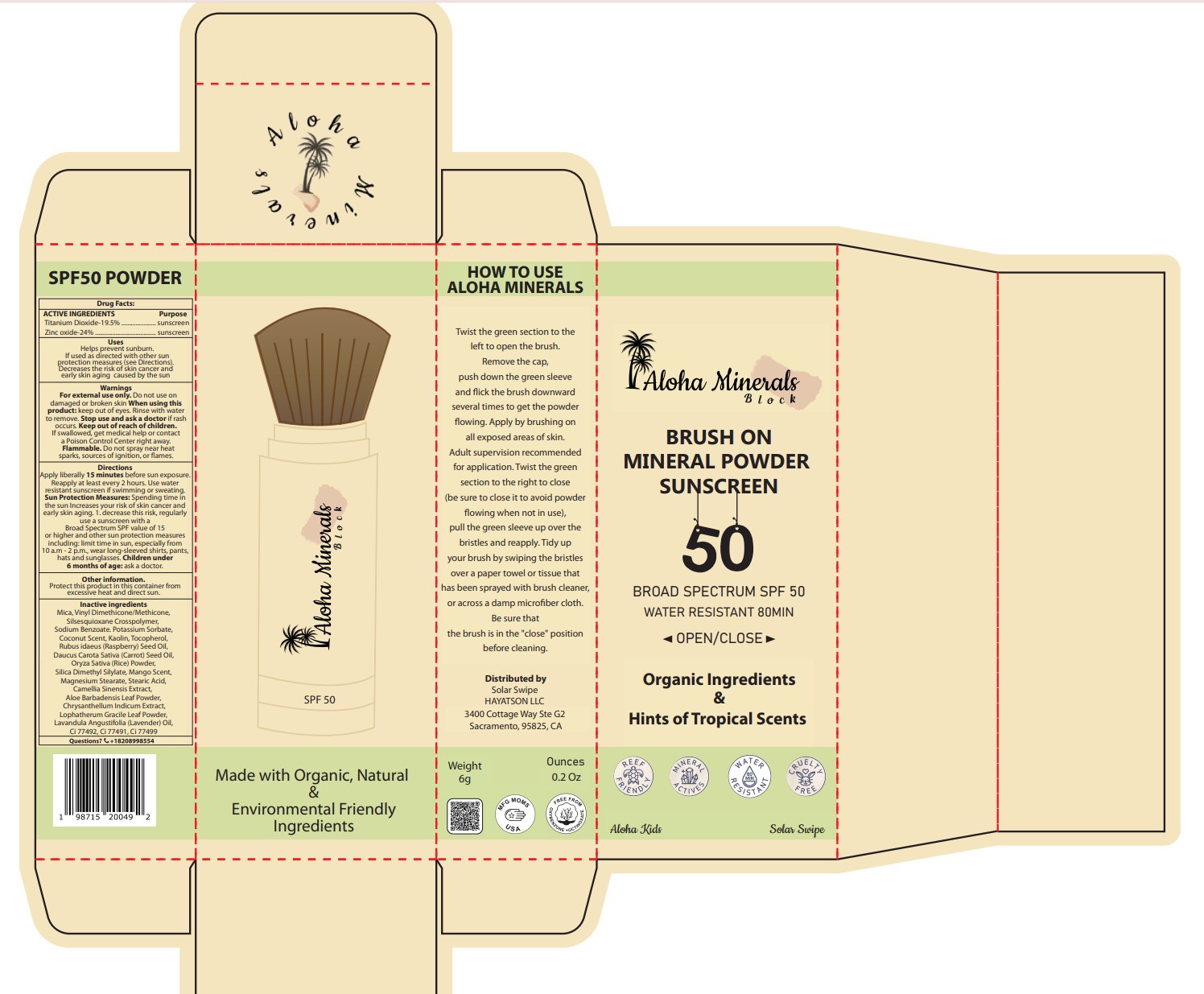 DRUG LABEL: Aloha mineral block-BRUSH ON MINERAL Powder SUNSCREEN SPF50
NDC: 82723-006 | Form: POWDER
Manufacturer: Aopline Health Industry Technology (Guangzhou) Co., Ltd.
Category: otc | Type: HUMAN OTC DRUG LABEL
Date: 20250108

ACTIVE INGREDIENTS: TITANIUM DIOXIDE 19.5 g/100 g; ZINC OXIDE 24 g/100 g
INACTIVE INGREDIENTS: FERROSOFERRIC OXIDE; MICA; VINYL DIMETHICONE/METHICONE SILSESQUIOXANE CROSSPOLYMER; STEARIC ACID; FERRIC OXIDE YELLOW; SODIUM BENZOATE; POTASSIUM SORBATE; COCONUT; RASPBERRY SEED OIL; CARROT SEED OIL; RICE BRAN; KAOLIN; SILICA DIMETHYL SILYLATE; MANGO; MAGNESIUM STEARATE; TOCOPHEROL; ALOE VERA LEAF; GREEN TEA LEAF; CHRYSANTHELLUM INDICUM TOP; LOPHATHERUM GRACILE LEAF; LAVENDER OIL; FERRIC OXIDE RED

82723-006
Aloha mineral block-BRUSH ON MINERAL POWDER SUNSCREEN SPF50

Active Ingredients

Titanium dioxide-19.5%

Zinc oxide-24%

Purpose

Sunscreen

Uses

Helps prevent sunburn. If used as directed with other sun protection measures (see Directions).Decreases the risk of skin cancer and early skin aging caused by the sun

Warnings

Flammable. Do not spray near heat sparks, sources of ignition, or flames.

When using this product: keep out of eyes. Rinse with water to remove. Stop use and ask a doctor if rash occurs. Keep out of reach of children. If swallowed, get medical help or contact a Poison Control Center right away.

Stop use

Stop use and ask a doctor if rash occurs.

ASK DOCTOR

Children under 6 months of age: ask a doctor.

Keep out of reach of children. If swallowed, get medical help or contact a Poison Control Center right away.

Directions

Apply liberally 15 minutes before sun exposure. Reapply at least every 2 hours. Use water

resistant sunscreen if swimming or sweating.

Other Information

Protect this product in this container from excessive heat and direct sun.

Inactive Ingredients

Mica, Vinyl Dimethicone/Methicone,Silsesquioxane Crosspolymer, Sodium Benzoate. Potassium Sorbate,Coconut Scent, Kaolin, Tocopherol,Rubus idaeus (Raspberry) Seed Oil, Daucus Carota Sativa (Carrot) Seed Oil,Oryza Sativa (Rice) Powder,Silica Dimethyl Silylate, Mango Scent,Magnesium Stearate, Stearic Acid,Camellia Sinensis Extract, Aloe Barbadensis Leaf Powder,Chrysanthellum Indicum Extract,Lophatherum Gracile Leaf Powder,Lavandula Angustifolia (Lavender) Oil,Ci 77492, Ci 77491, Ci 77499

Package Label

label 82723-006-01